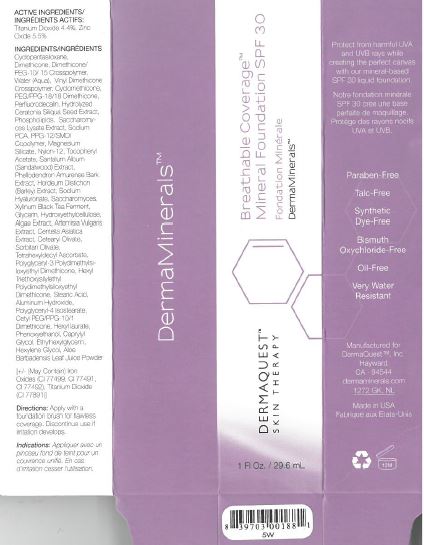 DRUG LABEL: Mineral Foundation SPF 30-5W
NDC: 62742-4099 | Form: CREAM
Manufacturer: Allure Labs Inc.
Category: otc | Type: HUMAN OTC DRUG LABEL
Date: 20171205

ACTIVE INGREDIENTS: ZINC OXIDE 55 mg/1 mL; TITANIUM DIOXIDE 44 mg/1 mL
INACTIVE INGREDIENTS: DIMETHICONE CROSSPOLYMER (450000 MPA.S AT 12% IN CYCLOPENTASILOXANE); DIMETHICONE; WATER; CYCLOMETHICONE; PEG/PPG-18/18 DIMETHICONE; PERFLUNAFENE; LECITHIN, SOYBEAN; SACCHAROMYCES LYSATE; SODIUM PYRROLIDONE CARBOXYLATE; PPG-12/SMDI COPOLYMER; MAGNESIUM SILICATE; NYLON-12; .ALPHA.-TOCOPHEROL ACETATE; SANDALWOOD; PHELLODENDRON AMURENSE BARK; BARLEY; HYALURONATE SODIUM; GLYCERIN; HYDROXYETHYL CELLULOSE (100 MPA.S AT 2%); ARTEMISIA VULGARIS ROOT; CENTELLA ASIATICA; CETEARYL OLIVATE; SORBITAN OLIVATE; TETRAHEXYLDECYL ASCORBATE; POLYGLYCERYL-3 POLYDIMETHYLSILOXYETHYL DIMETHICONE (4000 MPA.S); STEARIC ACID; ALUMINUM HYDROXIDE; POLYGLYCERYL-4 ISOSTEARATE; CETYL PEG/PPG-10/1 DIMETHICONE (HLB 2); HEXYL LAURATE; PHENOXYETHANOL; CAPRYLYL GLYCOL; ETHYLHEXYLGLYCERIN; HEXYLENE GLYCOL; ALOE VERA LEAF

Drug Facts

Active Ingredients:

Zinc Oxide - 5.5%

Titanium Dioxide - 4.4%

INDICATIONS AND USAGE

Direction: Apply with a foundation brush for flawless coverage. Discontinue use if irritation develpos.

DOSAGE AND ADMINISTRATION

Directions: Apply with a foundation brush for flawless coverage. Discontinue use if irritation develops.

PACKAGE LABEL

Manufactured for DermaQuest Inc.

Hayward, CA 94544

dermaminerals.com

1272 GK, NL

Made in USA